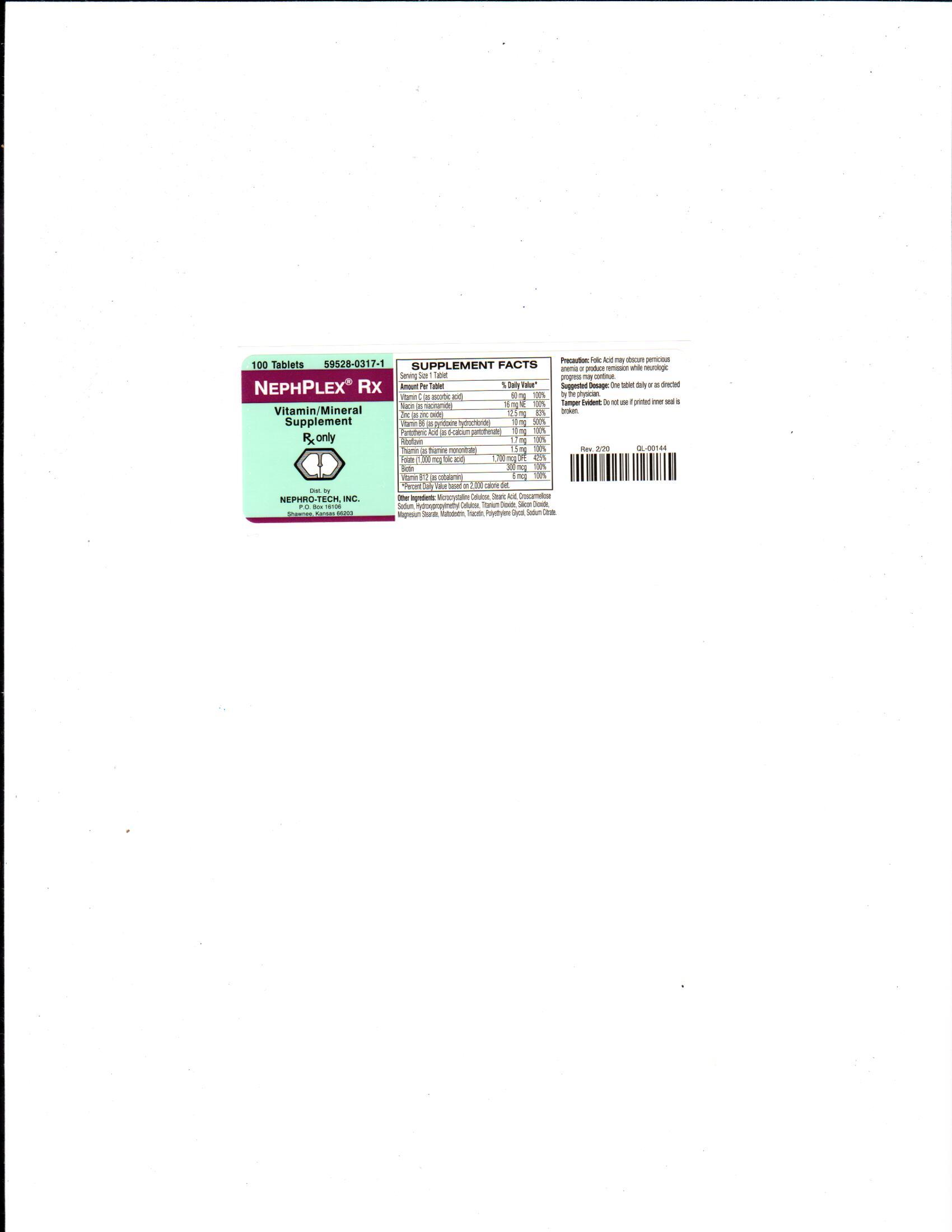 DRUG LABEL: NephPlex Rx
NDC: 59528-0317 | Form: TABLET, COATED
Manufacturer: Nephro-Tech, Inc.
Category: prescription | Type: HUMAN PRESCRIPTION DRUG LABEL
Date: 20210713

ACTIVE INGREDIENTS: ASCORBIC ACID 60 mg/1 1; NIACINAMIDE 20 mg/1 1; ZINC OXIDE 12.5 mg/1 1; PYRIDOXINE HYDROCHLORIDE 10 mg/1 1; PANTOTHENIC ACID 10 mg/1 1; RIBOFLAVIN 1.7 mg/1 1; THIAMINE 1.5 mg/1 1; FOLIC ACID 1 mg/1 1; BIOTIN .3 mg/1 1; COBALAMIN .006 mg/1 1

NephPlex Rx

Description

NephPlex Rx is a prescription folic acid supplement with additional nutrients for kidney dialysis patients. NephPlex Rx is a white, film-coated, oval shaped tablet.

Suggested Dosage

One tablet daily or as directed by the physician.

Precaution

Folic Acid may obscure pernicious anemia or produce remission while neurologic progress may continue.

Package Label/Prinicpal Display Panel

59528-0317-1

Rx Only

NephPlex Rx

Vitamin/Mineral Supplement

100 tablets